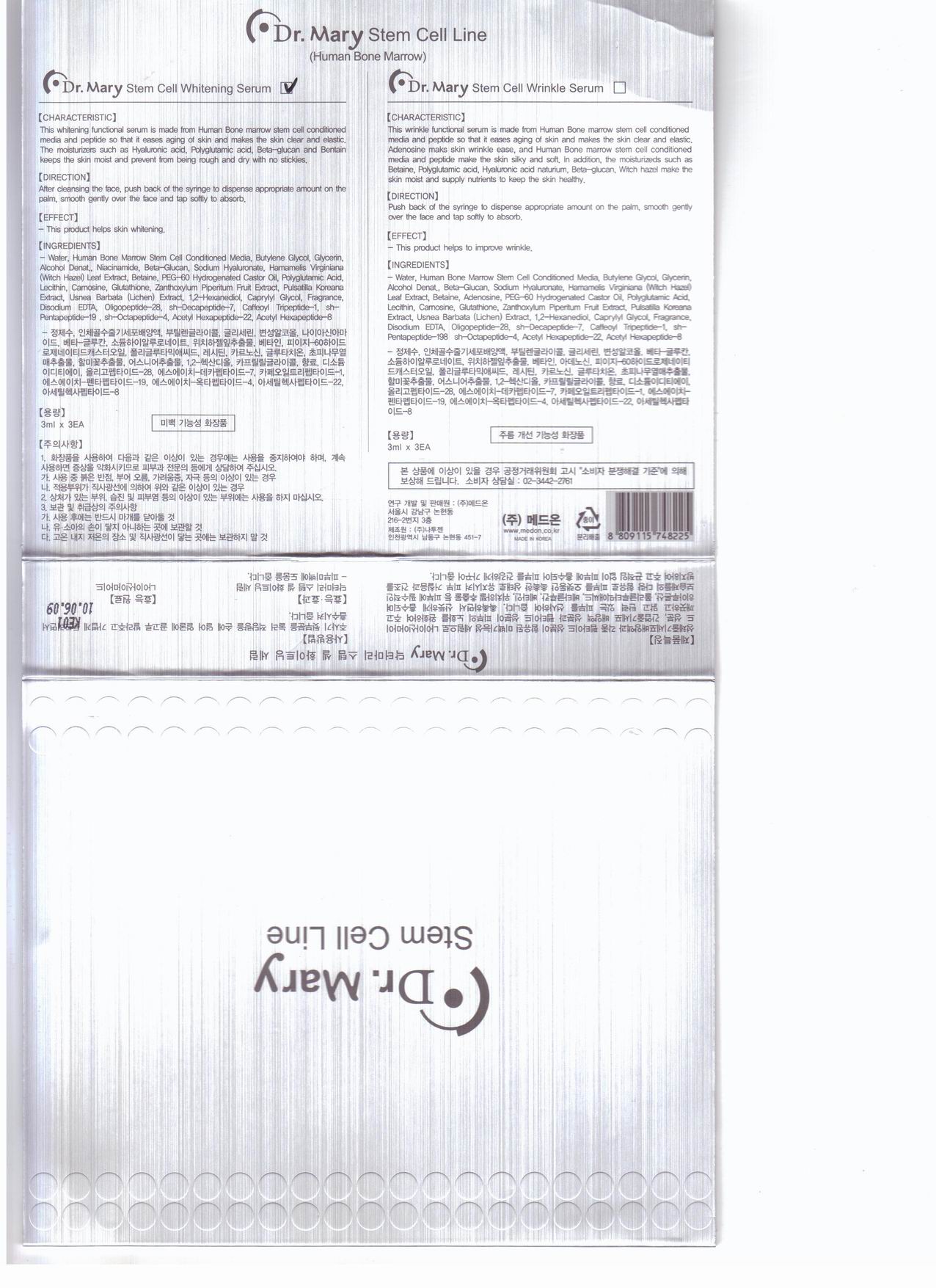 DRUG LABEL: Stem Cell Wrinkle Serum
NDC: 76071-2001 | Form: LIQUID
Manufacturer: Medon Co., Ltd
Category: otc | Type: HUMAN OTC DRUG LABEL
Date: 20110406

ACTIVE INGREDIENTS: ADENOSINE 0.0004 mL/1 mL
INACTIVE INGREDIENTS: BUTYLENE GLYCOL; GLYCERIN; ALCOHOL; BETADEX; HYALURONATE SODIUM; HAMAMELIS VIRGINIANA BARK; BETAINE; POLYOXYL 60 HYDROGENATED CASTOR OIL; LECITHIN, SOYBEAN; CARNOSINE; GLUTATHIONE; ZANTHOXYLUM PIPERITUM FRUIT PULP; USNEA BARBATA; CAPRYLYL GLYCOL; EDETATE DISODIUM

Drug Facts

active ingredient: adenosine

inactive ingredient: water, human bone marrow stem cell conditioned media, butylene glycol, glycerin, alcohol denat, beta-glucan, sodium hyaluronate, hamamelis virginiana leaf extract, betaine, peg-60 hydrogenated castor oil, polyglutamic acid, lecithin, carnosine, glutathione, zanthoxylum piperitum fruit extract, pulsatilla koreana extract, usnea barbata extract, 1,2-hexanediol, caprylyl glycol, fragrance, disodium edta, oligopeptide-28, sh-decapeptide-7, caffeoyl tripeptide-1, sh-pentapeptide-198, sh-octapeptide-4, acetyl hexapeptide-22, acetyl hexapeptide-8

PURPOSE

to improve wrinkle

keep out of reach of the children

INDICATIONS AND USAGE

- cleansing the skin
- dispense an amount on the palm
- smooth gently over the face and tap softly to absorb

- do not use when you feel itching
- do not swallow
- clean the skin before use

DOSAGE AND ADMINISTRATION

for external use only